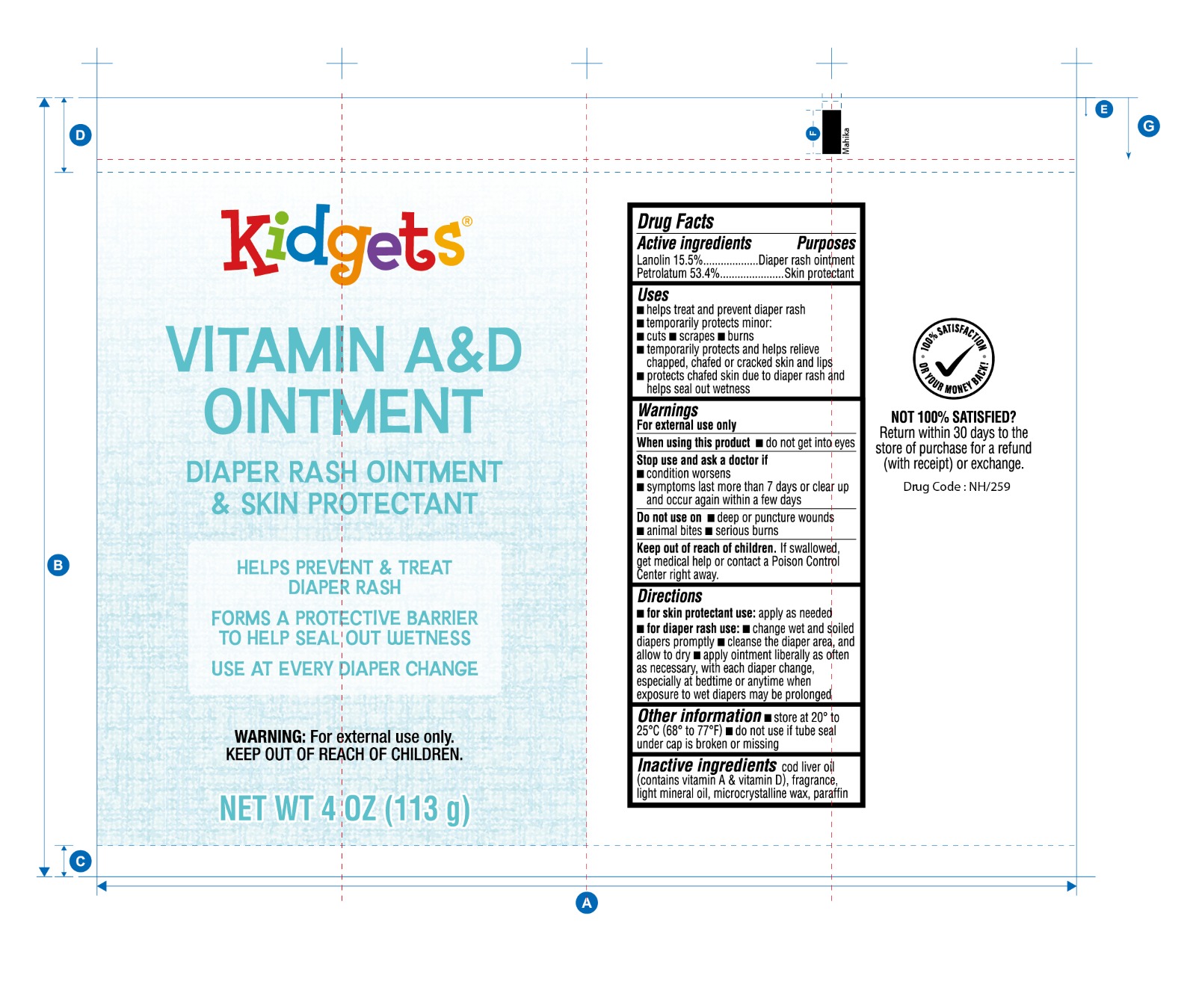 DRUG LABEL: Vitamin A and D
NDC: 55319-603 | Form: OINTMENT
Manufacturer: MIDWOOD BRANDS, LLC
Category: otc | Type: HUMAN OTC DRUG LABEL
Date: 20240718

ACTIVE INGREDIENTS: PETROLATUM 53.4 g/100 g; LANOLIN 15.5 g/100 g
INACTIVE INGREDIENTS: MICROCRYSTALLINE WAX; COD LIVER OIL; FRAGRANCE 13576; LIGHT MINERAL OIL; PARAFFIN

Vitamin A&D Ointment

Active Ingredients

Lanolinn - 15.5%

Petrolatum - 53.4%

Purpose

Skin protectant

Uses

- helps treat and prevent diaper rash
- temporarily protects minor cuts, scrapes and burns
- temporarily protects and helps relieve chapped, chafed or cracked skin and lips
- protects chafed skin due to diaper rash and helps seal out wetness

Warnings

For external use only

Do not use in eyes

- not for extensive burns or serious cuts, consult a physician

Stop use and ask a doctorif redness, irritation, swelling or pain persists or increases or if infection develops.

Keep out of reach of children.

If swallowed, get medical help or contact a Poison Control Center right away.

Directions

- Apply generously and massage until absorbed. Repeat as necessary.

Inactive Ingredients

Cod Liver Oil
Fragrance
Light Mineral Oil

Microcrystalin Wax

Water

PACKAGE LABEL

PRINCIPAL DISPLAY PANEL

Vitamin A&D Cream

NET WT 4 OZ (113 g)